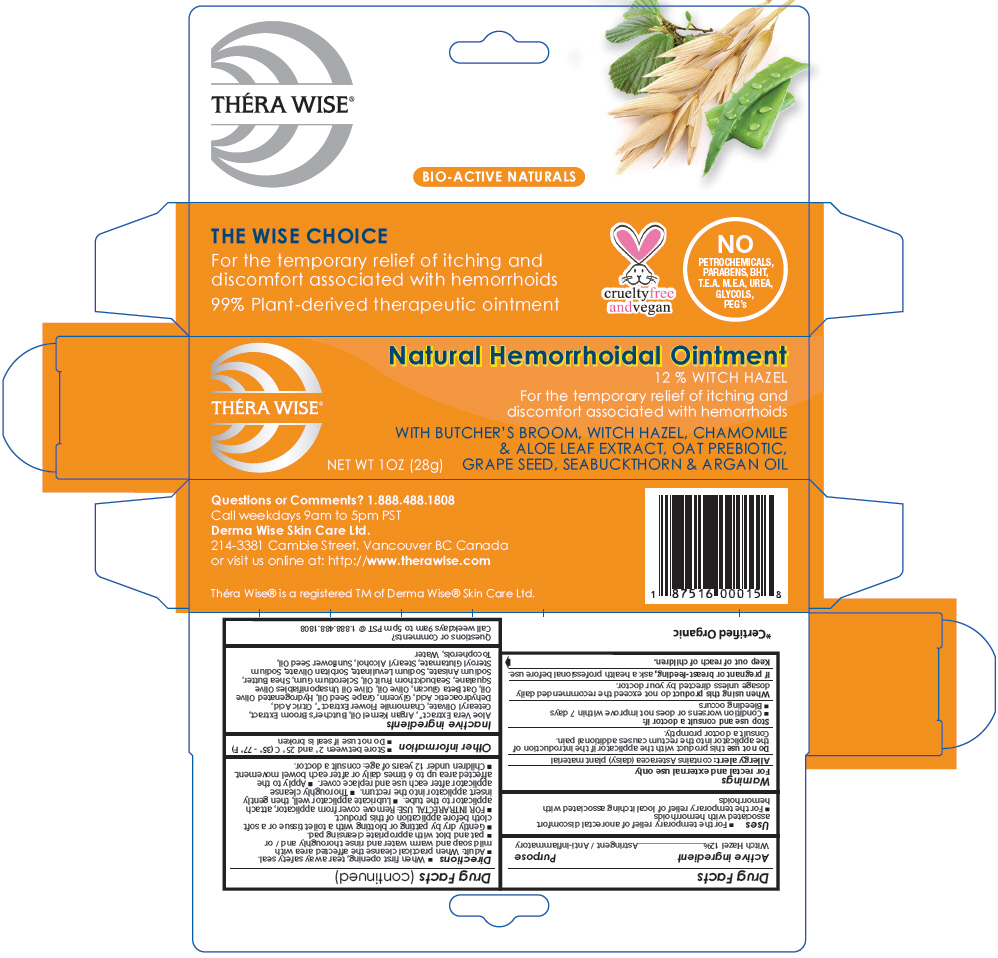 DRUG LABEL: Thera Wise Natural Hemorrhoidal
NDC: 43347-158 | Form: OINTMENT
Manufacturer: Derma Wise Skin Care Ltd.
Category: otc | Type: HUMAN OTC DRUG LABEL
Date: 20260106

ACTIVE INGREDIENTS: Witch Hazel 3.36 g/28 g
INACTIVE INGREDIENTS: Aloe Vera Leaf; Ruscus Aculeatus Root; Cetearyl Olivate; Chamaemelum Nobile Flower; Citric Acid Monohydrate; Dehydroacetic acid; Glycerin; Grape Seed Oil; Hydrogenated Olive Oil; Olive Oil; Olea Europaea (Olive) Oil Unsaponifiables; Squalane; Betasizofiran; Shea Butter; Sodium Anisate; Sodium Levulinate; Sorbitan Olivate; Sodium Stearoyl Glutamate; Stearyl Alcohol; Sunflower Oil; Tocopherol; Glucosyl Hesperidin; Water

Théra Wise® Natural Hemorrhoidal

Drug Facts

Active ingredient

Witch Hazel 12%

Purpose

Astringent / Anti-inflammatory

Uses

- For the temporary relief of anorectal discomfort associated with hemorrhoids
- For the temporary relief of local itching associated with hemorrhoids

Warnings

For rectal and external use only

Allergy alert: contains Asteracea (daisy) plant material

Do not use this product with the applicator if the introduction of the applicator into the rectum causes additional pain.

Consult a doctor promptly.

Stop use and consult a doctor if:

- Condition worsens or does not improve within 7 days
- Bleeding occurs

When using this product do not exceed the recommended daily dosage unless directed by your doctor.

PREGNANCY OR BREAST FEEDING

If pregnant or breast-feeding, ask a health professional before use.

Keep out of reach of children.

Directions

- When first opening, tear away safety seal.
- Adult: When practical cleanse the affected area with mild soap and warm water and rinse thoroughly and / or
- pat and blot with appropriate cleansing pad.
- Gently dry by patting or blotting with a toilet tissue or a soft cloth before application of this product.
- FOR INTRARECTAL USE: Remove cover from applicator, attach applicator to the tube.
- Lubricate applicator well, then gently insert applicator into the rectum.
- Thoroughly cleanse applicator after each use and replace cover.
- Apply to the affected area up to 6 times daily or after each bowel movement.
- Children under 12 years of age: consult a doctor.

Other information

- Store between 2° and 25° C (35° - 77° F)
- Do not use if seal is broken

Inactive ingredients

Aloe Vera Extract [Certified Organic] , Argan Kernel Oil, Butcher's Broom Extract, Cetearyl Olivate, Chamomile Flower Extract, Citric Acid, Dehydroacetic Acid, Glycerin, Grape Seed Oil, Hydrogenated Olive Oil, Oat Beta Glucan, Olive Oil, Olive Oil Unsaponifiables Olive Squalane, Seabuckthorn Fruit Oil, Sclerotium Gum, Shea Butter, Sodium Anisate, Sodium Levulinate, Sorbitan Olivate, Sodium Steroyl Glutamate, Stearyl Alcohol, Sunflower Seed Oil, Tocopherols, Water

Questions or Comments?

Call weekdays 9am to 5pm PST @ 1.888.488.1808

PRINCIPAL DISPLAY PANEL - 28 g Tube Box

Natural Hemorrhoidal Ointment

12 % WITCH HAZEL
For the temporary relief of itching and
discomfort associated with hemorrhoids

THÉRA WISE®

WITH BUTCHER'S BROOM, WITCH HAZEL, CHAMOMILE
& ALOE LEAF EXTRACT, OAT PREBIOTIC,
GRAPE SEED, SEABUCKTHORN & ARGAN OIL

NEW WT 1OZ (28g)